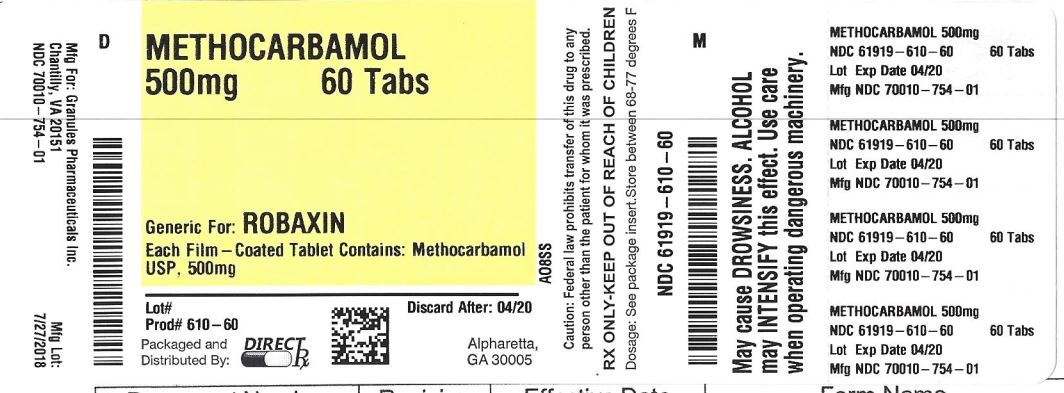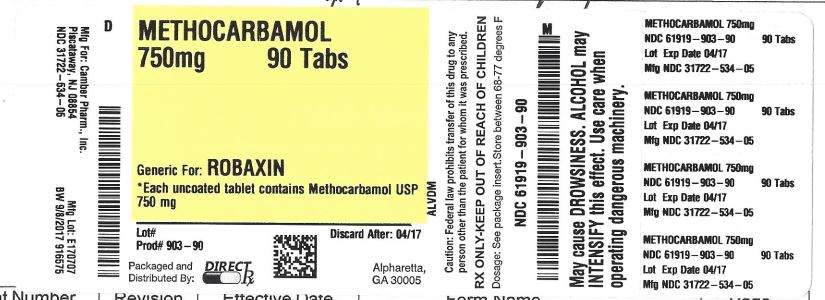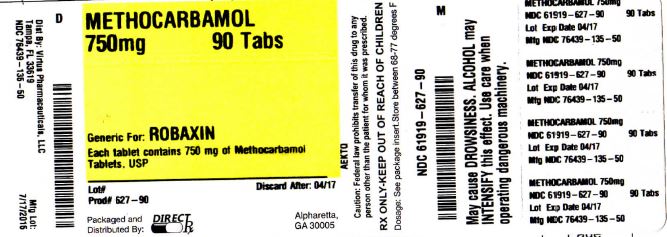 DRUG LABEL: METHOCARBAMOL
NDC: 61919-627 | Form: TABLET, FILM COATED
Manufacturer: DirectRX
Category: prescription | Type: HUMAN PRESCRIPTION DRUG LABEL
Date: 20190423

ACTIVE INGREDIENTS: METHOCARBAMOL 750 mg/1 1
INACTIVE INGREDIENTS: CROSCARMELLOSE SODIUM; FERRIC OXIDE YELLOW; FERRIC OXIDE RED; HYDROXYPROPYL CELLULOSE (1600000 WAMW); HYPROMELLOSES; MAGNESIUM STEARATE; POLYETHYLENE GLYCOL, UNSPECIFIED; TRIACETIN; TITANIUM DIOXIDE; CELLULOSE, MICROCRYSTALLINE

METHOCARBAMOL

Special Populations

The clearance of methocarbamol in 8 renally-impaired patients on maintenance hemodialysis was reduced about 40% compared to 17 normal subjects, although the mean (± SD) elimination half-life in these two groups was similar: 1.2 (± 0.6) versus 1.1 (± 0.3) hours, respectively.